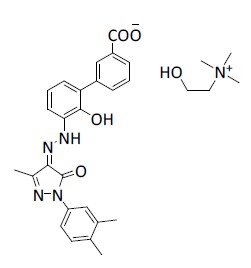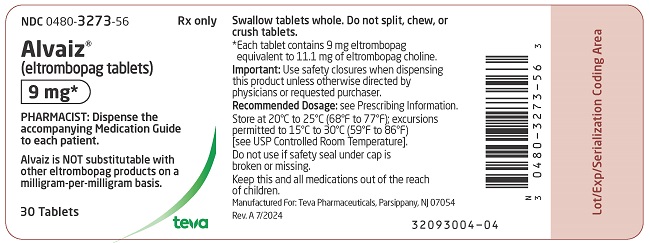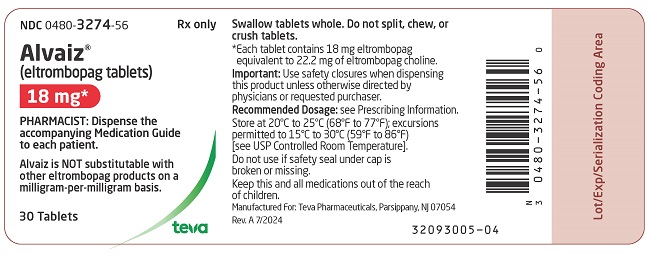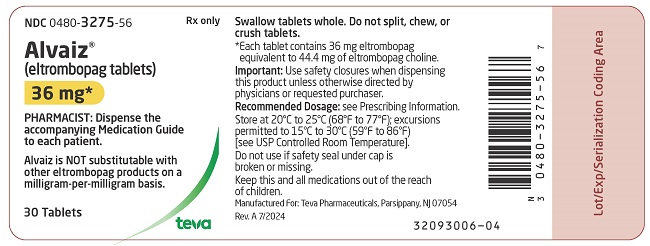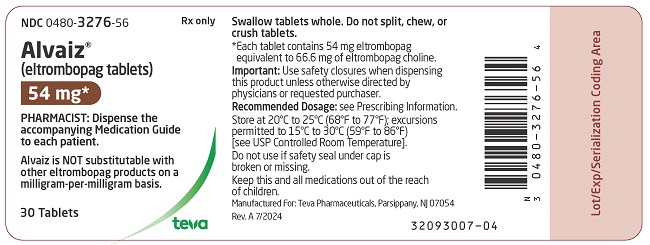 DRUG LABEL: ALVAIZ
NDC: 0480-3273 | Form: TABLET, FILM COATED
Manufacturer: Teva Pharmaceuticals, Inc.
Category: prescription | Type: HUMAN PRESCRIPTION DRUG LABEL
Date: 20260130

ACTIVE INGREDIENTS: ELTROMBOPAG CHOLINE 9 mg/1 1
INACTIVE INGREDIENTS: ANHYDROUS LACTOSE; COPOVIDONE K25-31; CROSCARMELLOSE SODIUM; EDETATE DISODIUM; MAGNESIUM STEARATE; POLOXAMER 188; POLYETHYLENE GLYCOL 4000; POVIDONE K12; MICROCRYSTALLINE CELLULOSE; SILICON DIOXIDE; FD&C BLUE NO. 1 ALUMINUM LAKE; POLYETHYLENE GLYCOL 3350; POLYVINYL ALCOHOL, UNSPECIFIED; TALC; TITANIUM DIOXIDE

HIGHLIGHTS OF PRESCRIBING INFORMATION

These highlights do not include all the information needed to use ALVAIZ safely and effectively. See full prescribing information for ALVAIZ.
ALVAIZ® (eltrombopag tablets), for oral use
Initial U.S. Approval: 2008

WARNING: RISK FOR HEPATIC DECOMPENSATION IN PATIENTS WITH CHRONIC HEPATITIS C and RISK OF HEPATOTOXICITY

See full prescribing information for complete boxed warning.

In patients with chronic hepatitis C, ALVAIZ in combination with interferon and ribavirin may increase the risk of hepatic decompensation. (5.1)

ALVAIZ may increase the risk of severe and potentially life-threatening hepatotoxicity. Monitor hepatic function and discontinue dosing as recommended. (5.2)

RECENT MAJOR CHANGES

Warnings and Precautions, Laboratory Test Interference (5.6) 7/2025

1 INDICATIONS AND USAGE

ALVAIZ is a thrombopoietin receptor agonist indicated:

- for the treatment of thrombocytopenia in adult and pediatric patients 6 years and older with persistent or chronic immune thrombocytopenia (ITP) who have had an insufficient response to corticosteroids, immunoglobulins, or splenectomy. ALVAIZ should be used only in patients with ITP whose degree of thrombocytopenia and clinical condition increase the risk for bleeding. (1.1)
- for the treatment of thrombocytopenia in adult patients with chronic hepatitis C to allow the initiation and maintenance of interferon-based therapy. ALVAIZ should be used only in patients with chronic hepatitis C whose degree of thrombocytopenia prevents the initiation of interferon-based therapy or limits the ability to maintain interferon-based therapy. (1.2)
- for the treatment of adult patients with severe aplastic anemia who have had an insufficient response to immunosuppressive therapy. (1.3)

Limitations of Use:

- ALVAIZ is not indicated for the treatment of patients with myelodysplastic syndrome (MDS). (1.4)
- Safety and efficacy have not been established in combination with direct-acting antiviral agents used without interferon for treatment of chronic hepatitis C infection. (1.4)

2 DOSAGE AND ADMINISTRATION

- ALVAIZ is not substitutable with other eltrombopag products on a milligram per milligram basis. (2.1)

- Take ALVAIZ without a meal or with a meal low in calcium (≤ 50 mg). Take ALVAIZ at least 2 hours before or 4 hours after any medications or products containing polyvalent cations, such as antacids, calcium-rich foods, and mineral supplements. (2.4, 7.1, 12.3)
- Persistent or Chronic ITP: Initiate ALVAIZ at 36 mg orally once daily for most adult and pediatric patients 6 years and older. Dose reductions are needed for patients with hepatic impairment and some patients of East-/Southeast-Asian ancestry. Adjust to maintain platelet count greater than or equal to 50 x 10^9/L. Do not exceed 54 mg per day. (2.1, 8.6, 8.7)
- Chronic Hepatitis C-associated Thrombocytopenia: Initiate ALVAIZ at 18 mg orally once daily for all patients. Adjust to achieve target platelet count required to initiate antiviral therapy. Do not exceed a daily dose of 72 mg. (2.2)
- Refractory Severe Aplastic Anemia: Initiate ALVAIZ at 36 mg orally once daily. Reduce initial dose in patients with hepatic impairment or patients of East-/Southeast-Asian ancestry. Adjust to maintain platelet count greater than 50 x 10^9/L. Do not exceed 108 mg per day. (2.3, 8.6, 8.7)

3 DOSAGE FORMS AND STRENGTHS

Tablets: 9 mg, 18 mg, 36 mg, and 54 mg (3)

4 CONTRAINDICATIONS

None. (4)

5 WARNINGS AND PRECAUTIONS

- Hepatotoxicity: Monitor liver function before and during therapy. (5.2)
- Increased Risk of Death and Progression of Myelodysplastic Syndromes to Acute Myeloid Leukemia. (5.3)
- Thrombotic/Thromboembolic Complications: Portal vein thrombosis has been reported in patients with chronic liver disease receiving eltrombopag. Monitor platelet counts regularly. (5.4)

6 ADVERSE REACTIONS

Across all indications, the most common adverse reactions (≥ 20% in any indication) were: anemia, nausea, pyrexia, alanine aminotransferase increased, cough, fatigue, headache, and diarrhea. (6.1)

To report SUSPECTED ADVERSE REACTIONS, contact Teva at 1-888-838-2872 or FDA at 1-800-FDA-1088 or www.fda.gov/medwatch.

8 USE IN SPECIFIC POPULATIONS

Lactation: Advise women not to breastfeed during treatment. (8.2)

FULL PRESCRIBING INFORMATION

WARNING: RISK FOR HEPATIC DECOMPENSATION IN PATIENTS WITH CHRONIC HEPATITIS C and RISK OF HEPATOTOXICITY

In patients with chronic hepatitis C, ALVAIZ in combination with interferon and ribavirin may increase the risk of hepatic decompensation [see Warnings and Precautions (5.1)].

ALVAIZ may increase the risk of severe and potentially life-threatening hepatotoxicity. Monitor hepatic function and discontinue dosing as recommended [see Warnings and Precautions (5.2)].

RECENT MAJOR CHANGES

Warnings and Precautions, Laboratory Test Interference (5.6) 6/2025

1 INDICATIONS AND USAGE

1.1 Treatment of Thrombocytopenia in Patients with Persistent or Chronic Immune Thrombocytopenia

ALVAIZ® (eltrombopag tablets) are indicated for the treatment of thrombocytopenia in adult and pediatric patients 6 years and older with persistent or chronic immune thrombocytopenia (ITP) who have had an insufficient response to corticosteroids, immunoglobulins, or splenectomy. ALVAIZ should be used only in patients with ITP whose degree of thrombocytopenia and clinical condition increase the risk for bleeding.

1.2 Treatment of Thrombocytopenia in Patients with Hepatitis C Infection

ALVAIZ is indicated for the treatment of thrombocytopenia in adult patients with chronic hepatitis C to allow the initiation and maintenance of interferon-based therapy. ALVAIZ should be used only in patients with chronic hepatitis C whose degree of thrombocytopenia prevents the initiation of interferon-based therapy or limits the ability to maintain interferon-based therapy.

1.3 Treatment of Severe Aplastic Anemia

ALVAIZ is indicated for the treatment of adult patients with severe aplastic anemia who have had an insufficient response to immunosuppressive therapy.

1.4 Limitations of Use

- ALVAIZ is not indicated for the treatment of patients with myelodysplastic syndromes (MDS) [see Warnings and Precautions (5.3)].
- Safety and efficacy have not been established in combination with direct-acting antiviral agents used without interferon for treatment of chronic hepatitis C infection.

2 DOSAGE AND ADMINISTRATION

2.1 Important Dosage Information

- Eltrombopag is available for different indications and in different dosage forms and tablet strengths.
- ALVAIZ is not substitutable with other eltrombopag products on a milligram per milligram basis due to the observed bioavailability in studies conducted on ALVAIZ.
- Patients must be able to swallow ALVAIZ tablets whole [see Dosage and Administration (2.5)].

2.2 Recommended Dosage for Persistent or Chronic Immune Thrombocytopenia

Use the lowest dose of ALVAIZ to achieve and maintain a platelet count greater than or equal to 50 x 10^9/L as necessary to reduce the risk for bleeding. Dose adjustments are based upon the platelet count response. Do not use ALVAIZ to normalize platelet counts [see Warnings and Precautions (5.4)]. In clinical trials, platelet counts generally increased within 1 to 2 weeks after starting ALVAIZ and decreased within 1 to 2 weeks after discontinuing ALVAIZ [see Clinical Studies (14.1)].

Initial Dose Regimen: Adult and Pediatric Patients 6 Years and Older with ITP: Initiate ALVAIZ at a dose of 36 mg orally once daily, except in patients who are of East-/Southeast-Asian ancestry or who have mild to severe hepatic impairment (Child-Pugh Class A, B, C).

For patients of East-/Southeast-Asian ancestry with ITP, initiate ALVAIZ at a reduced dose of 18 mg orally once daily [see Use in Specific Populations (8.7), Clinical Pharmacology (12.3)].

For patients with ITP and mild, moderate, or severe hepatic impairment (Child-Pugh Class A, B, C), initiate ALVAIZ at a reduced dose of 18 mg orally once daily [see Use in Specific Populations (8.6), Clinical Pharmacology (12.3)].

For patients of East-/Southeast-Asian ancestry with ITP and hepatic impairment (Child-Pugh Class A, B, C), consider initiating ALVAIZ at a reduced dose of 9 mg orally once daily [see Clinical Pharmacology (12.3)].

Monitoring and Dose Adjustment: After initiating ALVAIZ, adjust the dose to achieve and maintain a platelet count greater than or equal to 50 x 10^9/L as necessary to reduce the risk for bleeding. Do not exceed a dose of 54 mg daily. Monitor clinical hematology and liver tests regularly throughout therapy with ALVAIZ and modify the dosage regimen of ALVAIZ based on platelet counts as outlined in Table 1. During therapy with ALVAIZ, assess complete blood counts (CBCs) with differentials, including platelet counts, weekly until a stable platelet count has been achieved. Obtain CBCs with differentials, including platelet counts, monthly thereafter.

Table 1. Dose Adjustments of ALVAIZ in Patients with Persistent or Chronic Immune Thrombocytopenia
Platelet Count Result | Dose Adjustment or Response
< 50 x 10^9/L following at least 2 weeks of ALVAIZ | Increase daily dose by 18 mg to a maximum of 54 mg/day.; For patients taking 9 mg once daily, increase the dose to 18 mg daily before increasing the dose amount by 18 mg.
≥ 200 x 10^9/L to ≤ 400 x; 10^9/L at any time | Decrease the daily dose by 18 mg. Wait 2 weeks to assess the effects of this and any subsequent dose adjustments.; For patients taking 18 mg once daily, decrease the dose to 9 mg once daily.
> 400 x 10^9/L | Stop ALVAIZ; increase the frequency of platelet monitoring to twice weekly.; Once the platelet count is < 150 x 10^9/L, reinitiate therapy at a daily dose reduced by 18 mg.; For patients taking 18 mg once daily, reinitiate therapy at a daily dose of 9 mg.
> 400 x 10^9/L after 2 weeks of therapy at lowest dose of ALVAIZ | Discontinue ALVAIZ.

In patients with ITP and hepatic impairment (Child-Pugh Class A, B, C), after initiating ALVAIZ or after any subsequent dosing increase, wait 3 weeks before increasing the dose.

Modify the dosage regimen of concomitant ITP medications, as medically appropriate, to avoid excessive increases in platelet counts during therapy with ALVAIZ. Do not administer more than one dose of ALVAIZ within any 24-hour period.

Discontinuation: Discontinue ALVAIZ if the platelet count does not increase to a level sufficient to avoid clinically important bleeding after 4 weeks of therapy with ALVAIZ at the maximum daily dose of 54 mg. Excessive platelet count responses, as outlined in Table 1, or important liver test abnormalities (e.g., transaminases and/or bilirubin) also necessitate discontinuation of ALVAIZ [see Warnings and Precautions (5.2, 5.6) and Drug Interactions (7.5)]. Obtain CBCs with differentials, including platelet counts, weekly for at least 4 weeks following discontinuation of ALVAIZ.

2.3 Recommended Dosage for Chronic Hepatitis C-associated Thrombocytopenia

Use the lowest dose of ALVAIZ to achieve and maintain a platelet count necessary to initiate and maintain antiviral therapy with pegylated interferon and ribavirin. Dose adjustments are based upon the platelet count response. Do not use ALVAIZ to normalize platelet counts [see Warnings and Precautions (5.4)]. In clinical trials, platelet counts generally began to rise within the first week of treatment with ALVAIZ [see Clinical Studies (14.2)].

Initial Dose Regimen: Initiate ALVAIZ at a dose of 18 mg orally once daily.

Monitoring and Dose Adjustment: Adjust the dose of ALVAIZ in 18-mg increments every 2 weeks as necessary to achieve the target platelet count required to initiate antiviral therapy. Monitor platelet counts every week prior to starting antiviral therapy.

During antiviral therapy, adjust the dose of ALVAIZ to avoid dose reductions of peginterferon. Monitor CBCs with differentials, including platelet counts, weekly during antiviral therapy until a stable platelet count is achieved. Monitor platelet counts monthly thereafter. Do not exceed a dose of 72 mg daily. Monitor clinical hematology and liver tests (e.g., transaminases and bilirubin) regularly throughout therapy with ALVAIZ [see Drug Interactions (7.5)].

For specific dosage instructions for peginterferon or ribavirin, refer to their respective prescribing information.

Table 2. Dose Adjustments of ALVAIZ in Adults with Thrombocytopenia Due to Chronic Hepatitis C
Platelet Count Result | Dose Adjustment or Response
< 50 x 10^9/L following at least 2 weeks of ALVAIZ | Increase daily dose by 18 mg to a maximum of 72 mg/day.
≥ 200 x 10^9/L to ≤ 400 x; 10^9/L at any time | Decrease the daily dose by 18 mg.; Wait 2 weeks to assess the effects of this and any subsequent dose adjustments.
> 400 x 10^9/L | Stop ALVAIZ; increase the frequency of platelet monitoring to twice weekly.; Once the platelet count is < 150 x 10^9/L, reinitiate therapy at a daily dose reduced by 18 mg.; For patients taking 18 mg once daily, reinitiate therapy at a daily dose of 9 mg.
> 400 x 10^9/L after 2 weeks of therapy at lowest dose of ALVAIZ | Discontinue ALVAIZ.

Discontinuation: The prescribing information for pegylated interferon and ribavirin include recommendations for antiviral treatment discontinuation for treatment futility. Refer to pegylated interferon and ribavirin prescribing information for discontinuation recommendations for antiviral treatment futility.

ALVAIZ should be discontinued when antiviral therapy is discontinued. Excessive platelet count responses, as outlined in Table 2, or important liver test abnormalities also necessitate discontinuation of ALVAIZ [see Warnings and Precautions (5.2)].

2.4 Recommended Dosage for Refractory Severe Aplastic Anemia

Use the lowest dose of ALVAIZ to achieve and maintain a hematologic response. Dose adjustments are based upon the platelet count. Hematologic response requires dose titration, generally up to 108 mg, and may take up to 16 weeks after starting ALVAIZ [see Clinical Studies (14.3)].

Initial Dose Regimen: Initiate ALVAIZ at a dose of 36 mg orally once daily.

For patients with severe aplastic anemia of East-/Southeast-Asian ancestry or those with mild, moderate, or severe hepatic impairment (Child-Pugh Class A, B, C), initiate ALVAIZ at a reduced dose of 18 mg once daily [see Use in Specific Populations (8.6, 8.7), Clinical Pharmacology (12.3)].

Monitoring and Dose Adjustment: Adjust the dose of ALVAIZ in 36-mg increments every 2 weeks as necessary to achieve the target platelet count greater than or equal to 50 x 10^9/L as necessary. Do not exceed a dose of 108 mg daily. Monitor clinical hematology and liver tests regularly throughout therapy with ALVAIZ and modify the dosage regimen of ALVAIZ based on platelet counts as outlined in Table 3.

Table 3. Dose Adjustments of ALVAIZ in Patients with Refractory Severe Aplastic Anemia
Platelet Count Result | Dose Adjustment or Response
< 50 x 10^9/L following at least 2 weeks of ALVAIZ | Increase daily dose by 36 mg to a maximum of 108 mg/day.; For patients taking 18 mg once daily, increase the dose to 36 mg daily before increasing the dose amount by 36 mg.
≥ 200 x 10^9/L to ≤ 400 x 10^9/L at any time | Decrease the daily dose by 36 mg. Wait 2 weeks to assess the effects of this and any subsequent dose adjustments.
> 400 x 10^9/L | Stop ALVAIZ for 1 week.; Once the platelet count is < 150 x 10^9/L, reinitiate therapy at a dose reduced by 36 mg.
> 400 x 10^9/L after 2 weeks of therapy at lowest dose of ALVAIZ | Discontinue ALVAIZ.

For patients who achieve tri-lineage response, including transfusion independence, lasting at least 8 weeks: the dose of ALVAIZ may be reduced by 50% [see Clinical Studies (14.3)]. If counts remain stable after 8 weeks at the reduced dose, then discontinue ALVAIZ and monitor blood counts. If platelet counts drop to less than 30 x 10^9/L, hemoglobin to less than 9 g/dL, or absolute neutrophil count (ANC) to less than 0.5 x 10^9/L, ALVAIZ may be reinitiated at the previous effective dose.

Discontinuation: If no hematologic response has occurred after 16 weeks of therapy with ALVAIZ, discontinue therapy. If new cytogenetic abnormalities are observed, consider discontinuation of ALVAIZ [see Adverse Reactions (6.1)]. Excessive platelet count responses (as outlined in Table 3) or important liver test abnormalities also necessitate discontinuation of ALVAIZ [see Warnings and Precautions (5.2)].

2.5 Administration

Administration of Tablets: Take ALVAIZ without a meal or with a meal low in calcium (≤ 50 mg). Take ALVAIZ at least 2 hours before or 4 hours after other medications (e.g., antacids), calcium-rich foods (containing > 50 mg calcium e.g., dairy products, calcium-fortified juices, and certain fruits and vegetables), or supplements containing polyvalent cations, such as iron, calcium, aluminum, magnesium, selenium, and zinc [see Drug Interactions (7.1), Clinical Pharmacology (12.3)].

Swallow tablets whole. Do not split, chew, or crush tablets and mix with food or liquids.

3 DOSAGE FORMS AND STRENGTHS

- 9 mg, round, biconvex, blue film-coated tablets, debossed with “TV” on one side and “Z9” on the other side.
- 18 mg, round, biconvex, off-white film-coated tablets debossed with “TV” on one side and “Z18” on the other side.
- 36 mg, round, biconvex, red film-coated tablets, debossed with “TV” on one side and “Z36” on the other side.
- 54 mg, round, biconvex, orange film-coated tablets, debossed with “TV” on one side and “Z54” on the other side.

4 CONTRAINDICATIONS

None.

5 WARNINGS AND PRECAUTIONS

5.1 Hepatic Decompensation in Patients with Chronic Hepatitis C

In patients with chronic hepatitis C, ALVAIZ in combination with interferon and ribavirin may increase the risk of hepatic decompensation. In two controlled clinical trials in patients with chronic hepatitis C and thrombocytopenia, ascites and encephalopathy occurred more frequently on the arm receiving treatment with eltrombopag plus antivirals (7%) than the placebo plus antivirals arm (4%). Patients with low albumin levels (less than 3.5 g/dL) or Model for End-Stage Liver Disease (MELD) score greater than or equal to 10 at baseline had a greater risk for hepatic decompensation on the arm receiving treatment with eltrombopag plus antivirals. Discontinue ALVAIZ if antiviral therapy is discontinued.

5.2 Hepatotoxicity

ALVAIZ may increase the risk of severe and potentially life-threatening hepatotoxicity [see Adverse Reactions (6.1)]. One patient (< 1%) with ITP treated with eltrombopag in clinical trials experienced drug-induced liver injury. Eleven patients (1%) with chronic hepatitis C treated with eltrombopag in clinical trials experienced drug-induced liver injury.

Treatment of ITP, Chronic Hepatitis C-associated Thrombocytopenia, and Refractory Severe Aplastic Anemia

Measure serum ALT, AST, and bilirubin prior to initiation of ALVAIZ, every 2 weeks during the dose adjustment phase, and monthly following establishment of a stable dose [see Drug Interactions (7.5)]. ALVAIZ inhibits UDP-glucuronosyltransferase (UGT)1A1 and organic anion-transporting polypeptide (OATP)1B1, which may lead to indirect hyperbilirubinemia. If bilirubin is elevated, perform fractionation. Evaluate abnormal serum liver tests with repeat testing within 3 to 5 days. If the abnormalities are confirmed, monitor serum liver tests weekly until resolved or stabilized. Discontinue ALVAIZ if ALT levels increase to greater than or equal to 3 x ULN in patients with normal liver function or greater than or equal to 3 x baseline (or greater than 5 x ULN, whichever is the lower) in patients with pre-treatment elevations in transaminases and are:

- progressively increasing, or
- persistent for greater than or equal to 4 weeks, or
- accompanied by increased direct bilirubin, or
- accompanied by clinical symptoms of liver injury or evidence for hepatic decompensation.

If the potential benefit for reinitiating treatment with ALVAIZ is considered to outweigh the risk for hepatotoxicity, then consider cautiously reintroducing ALVAIZ and measure serum liver tests weekly during the dose adjustment phase. Hepatotoxicity may reoccur if ALVAIZ is reinitiated. If liver test abnormalities persist, worsen, or recur, then permanently discontinue ALVAIZ.

5.3 Increased Risk of Death and Progression of Myelodysplastic Syndromes to Acute Myeloid Leukemia

A randomized, double-blind, placebo-controlled, multicenter trial in patients with International Prognostic Scoring System (IPSS) intermediate-1, intermediate-2 or high risk MDS with thrombocytopenia, receiving azacitidine in combination with either eltrombopag (n = 179) or placebo (n = 177) was terminated due to lack of efficacy and safety reasons, including increased progression to acute myeloid leukemia (AML). Patients received eltrombopag or placebo at a starting dose of 200 mg once daily, up to a maximum of 300 mg once daily, in combination with azacitidine for at least six cycles. The incidence of death (overall survival) was 32% (57/179) in the eltrombopag arm versus 29% (51/177) in the placebo arm (HR [95% CI] = 1.42 [0.97, 2.08], showing an increased relative risk of death in this trial by 42% in the eltrombopag arm). The incidence of progression to AML was 12% (21/179) in the eltrombopag arm versus 6% (10/177) in the placebo arm (HR [95% CI] = 2.66 [1.31, 5.41], showing an increased relative risk of progression to AML in this trial by 166% in the eltrombopag arm).

5.4 Thrombotic/Thromboembolic Complications

Thrombotic/thromboembolic complications may result from increases in platelet counts with ALVAIZ. Reported thrombotic/thromboembolic complications included both venous and arterial events and were observed at low and at normal platelet counts.

Consider the potential for an increased risk of thromboembolism when administering ALVAIZ to patients with known risk factors for thromboembolism (e.g., Factor V Leiden, ATIII deficiency, antiphospholipid syndrome, chronic liver disease). To minimize the risk for thrombotic/thromboembolic complications, do not use ALVAIZ in an attempt to normalize platelet counts. Follow the dose adjustment guidelines to achieve and maintain target platelet counts [see Dosage and Administration (2.1, 2.2, 2.3)].

In two controlled clinical trials in patients with chronic hepatitis C and thrombocytopenia, 3% (31/955) treated with eltrombopag experienced a thrombotic event compared with 1% (5/484) on placebo. The majority of events were of the portal venous system (1% in patients treated with eltrombopag versus less than 1% for placebo).

In a controlled trial in patients with chronic liver disease and thrombocytopenia not related to ITP undergoing elective invasive procedures (N = 292), the risk of thrombotic events was increased in patients treated with 75 mg of eltrombopag once daily. Seven thrombotic complications (six patients) were reported in the group that received eltrombopag and three thrombotic complications were reported in the placebo group (two patients). All of the thrombotic complications reported in the group that received eltrombopag were portal vein thrombosis (PVT). Symptoms of PVT included abdominal pain, nausea, vomiting, and diarrhea. Five of the six patients in the group that received eltrombopag experienced a thrombotic complication within 30 days of completing treatment with eltrombopag and at a platelet count above 200 x 10^9/L. The risk of portal venous thrombosis was increased in thrombocytopenic patients with chronic liver disease treated with 75 mg of eltrombopag once daily for 2 weeks in preparation for invasive procedures.

5.5 Cataracts

In the three controlled clinical trials in adults with persistent or chronic ITP, cataracts developed or worsened in 15 (7%) patients who received 50 mg of eltrombopag daily and 8 (7%) placebo-group patients. In the extension trial, cataracts developed or worsened in 11% of patients who underwent ocular examination prior to therapy with eltrombopag. In the two controlled clinical trials in patients with chronic hepatitis C and thrombocytopenia, cataracts developed or worsened in 8% of patients treated with eltrombopag and 5% of patients treated with placebo.

Cataracts were observed in toxicology studies of eltrombopag in rodents [see Nonclinical Toxicology (13.2)]. Perform a baseline ocular examination prior to administration of eltrombopag and, during therapy with eltrombopag, regularly monitor patients for signs and symptoms of cataracts.

5.6 Laboratory Test Interference

Eltrombopag (ALVAIZ) is highly colored and can cause patient sample discoloration, which can interfere with some clinical laboratory tests. Inaccurate test results that are inconsistent with clinical observations may occur for multiple clinical chemistry tests including bilirubin and creatinine. In addition, other lab tests may be impacted, including but not limited to total protein and albumin, and incorrect test results may be generated if there is eltrombopag in the patient’s specimen. Communicate to the lab conducting the testing if your patient is taking ALVAIZ. Re-testing using other methods may also help in determining the validity of the test results [see Drug Interactions (7.5)].

6 ADVERSE REACTIONS

The following clinically significant adverse reactions associated with ALVAIZ are described in other sections.

- Hepatic Decompensation in Patients with Chronic Hepatitis C [see Warnings and Precautions (5.1)]
- Hepatotoxicity [see Warnings and Precautions (5.2)]
- Increased Risk of Death and Progression of Myelodysplastic Syndromes to Acute Myeloid Leukemia [see Warnings and Precautions (5.3)]
- Thrombotic/Thromboembolic Complications [see Warnings and Precautions (5.4)]
- Cataracts [see Warnings and Precautions (5.5)]

6.1 Clinical Trials Experience

Because clinical trials are conducted under widely varying conditions, adverse reaction rates observed in the clinical trials of a drug cannot be directly compared with rates in the clinical trials of another drug and may not reflect the rates observed in practice.

The safety of ALVAIZ has been established based on adequate and well-controlled studies of eltrombopag olamine in adult and pediatric patients 6 years and older with persistent or chronic ITP, adult patients with chronic hepatitis C-associated thrombocytopenia, and adult patients with refractory severe aplastic anemia. Below is a display of the adverse reactions of eltrombopag olamine in these adequate and well-controlled studies.

Persistent or Chronic Immune Thrombocytopenia: Adults: In clinical trials, hemorrhage was the most common serious adverse reaction and most hemorrhagic reactions followed discontinuation of eltrombopag. Other serious adverse reactions included thrombotic/thromboembolic complications [see Warnings and Precautions (5.4)]. The data described below reflect exposure of eltrombopag to patients with persistent or chronic ITP aged 18 to 85 years, of whom 66% were female, in three placebo-controlled trials and one open-label extension trial [see Clinical Studies (14.1)]. Eltrombopag was administered to 330 patients for at least 6 months and 218 patients for at least 1 year.

Table 4 presents the most common adverse drug reactions (experienced by greater than or equal to 3% of patients receiving eltrombopag) from the three placebo-controlled trials, with a higher incidence in eltrombopag versus placebo.

Table 4. Adverse Reactions (≥ 3%) From Three Placebo-controlled Trials in Adults with Persistent or Chronic Immune Thrombocytopenia
Adverse Reaction | Eltrombopag 50 mg; n = 241; (%) | Placebo; n = 128; (%)
Nausea | 9 | 3
Diarrhea | 9 | 7
Upper respiratory tract infection | 7 | 6
Vomiting | 6 | < 1
Urinary tract infectiona | 5 | 4
Increased ALT | 5 | 3
Myalgia | 5 | 2
Oropharyngeal pain | 4 | 3
Increased AST | 4 | 2
Pharyngitis | 4 | 2
Back pain | 3 | 2
Influenza | 3 | 2
Paresthesia | 3 | 2
Rash | 3 | 2
Abbreviations: ALT, alanine aminotransferase; AST, aspartate aminotransferase.
aIncludes PTs of urinary tract infection, cystitis, urinary tract infection bacterial, and bacteriuria.

In the three controlled clinical persistent or chronic ITP trials, alopecia, musculoskeletal pain, blood alkaline phosphatase increased, and dry mouth were the adverse reactions reported in 2% of patients treated with eltrombopag and in no patients who received placebo.

Among 302 patients with persistent or chronic ITP who received eltrombopag in the single-arm extension trial, the adverse reactions occurred in a pattern similar to that seen in the placebo-controlled trials. Table 5 presents the most common treatment-related adverse reactions (experienced by greater than or equal to 3% of patients receiving eltrombopag) from the extension trial.

Table 5. Treatment-related Adverse Reactions (≥3%) From Extension Trial in Adults with Persistent or Chronic Immune Thrombocytopenia
Adverse Reaction | Eltrombopag 50 mg; n = 302; (%)
Headache | 10
ALT increased | 5
AST increased | 5
Cataract | 5
Fatigue | 5
Blood bilirubin increased | 4
Nausea | 4
Hyperbilirubinemia | 3
Diarrhea | 3

Abbreviations: ALT, alanine aminotransferase; AST, aspartate aminotransferase.

In the three controlled persistent or chronic ITP trials, serum liver test abnormalities (predominantly Grade 2 or less in severity) were reported in 11% and 7% of patients for eltrombopag and placebo, respectively. Four patients (1%) treated with eltrombopag and three patients in the placebo group (2%) discontinued treatment due to hepatobiliary laboratory abnormalities. Seventeen of the patients treated with eltrombopag in the controlled trials with hepatobiliary laboratory abnormalities were re-exposed to eltrombopag in the extension trial. Eight of these patients again experienced liver test abnormalities (less than or equal to Grade 3) resulting in discontinuation of eltrombopag in one patient. In the extension persistent or chronic ITP trial, six additional patients had eltrombopag discontinued due to liver test abnormalities (less than or equal to Grade 3).

In the three controlled persistent or chronic ITP trials, cataracts developed or worsened in 7% of patients treated with eltrombopag and 7% of patients in the placebo group. All patients had documented, preexisting risk factors for cataractogenesis, including corticosteroid use. In the extension trial, cataracts developed or worsened in 11% of patients who underwent ocular examination prior to therapy with eltrombopag. Seventy-two percent of patients had preexisting risk factors, including corticosteroid use.

The safety of eltrombopag was also assessed in all patients treated in 7 adult persistent or chronic ITP clinical trials (N = 763 eltrombopag-treated patients and 179 placebo-treated patients). Thromboembolic events were reported in 6% of eltrombopag-treated patients versus 0% of placebo-treated patients and thrombotic microangiopathy with acute renal failure was reported in < 1% of eltrombopag-treated patients versus 0% of placebo-treated patients.

In a placebo-controlled trial of eltrombopag in patients with chronic liver disease and thrombocytopenia not related to ITP, six patients treated with eltrombopag and one patient in the placebo group developed portal vein thromboses [see Warnings and Precautions (5.4)].

Pediatric Patients: The data described below reflect median exposure to eltrombopag of 91 days for 107 pediatric patients (aged 1 to 17 years) with persistent or chronic ITP, of whom 53% were female, across the randomized phase of two placebo-controlled trials. ALVAIZ is not indicated for pediatric patients <6 years of age with persistent or chronic ITP.

Table 6 presents the most common adverse drug reactions (experienced by greater than or equal to 3% of pediatric patients 1 year and older receiving eltrombopag) across the two placebo-controlled trials, with a higher incidence for eltrombopag versus placebo.

Table 6. Adverse Reactions (≥ 3%) with a Higher Incidence for Eltrombopag Versus Placebo from Two Placebo-controlled Trials in Pediatric Patients 1 Year and Older with Persistent or Chronic Immune Thrombocytopenia
Adverse Reaction | Eltrombopag; n = 107; (%) | Placebo; n = 50; (%)
Upper respiratory tract infection | 17 | 6
Nasopharyngitis | 12 | 4
Cough | 9 | 0
Diarrhea | 9 | 2
Pyrexia | 9 | 8
Abdominal pain | 8 | 4
Oropharyngeal pain | 8 | 2
Toothache | 6 | 0
ALT increaseda | 6 | 0
Rash | 5 | 2
AST increased | 4 | 0
Rhinorrhea | 4 | 0
Abbreviations: ALT, alanine aminotransferase; AST, aspartate aminotransferase.
a Includes adverse reactions or laboratory abnormalities > 3 x ULN.

In the two controlled clinical persistent or chronic ITP trials, cataracts developed or worsened in 2 (1%) patients treated with eltrombopag. Both patients had received chronic oral corticosteroids, a risk factor for cataractogenesis.

Chronic Hepatitis C-associated Thrombocytopenia: In the two placebo-controlled trials, 955 patients with chronic hepatitis C-associated thrombocytopenia received eltrombopag. Table 7 presents the most common adverse drug reactions (experienced by greater than or equal to 10% of patients receiving eltrombopag compared with placebo).

Table 7. Adverse Reactions (≥ 10% and Greater Than Placebo) from Two Placebo-controlled Trials in Adults with Chronic Hepatitis C
Adverse Reaction | Eltrombopag; + Peginterferon/Ribavirin; n = 955; (%) | Placebo; + Peginterferon/Ribavirin; n = 484; (%)
Anemia | 40 | 35
Pyrexia | 30 | 24
Fatigue | 28 | 23
Headache | 21 | 20
Nausea | 19 | 14
Diarrhea | 19 | 11
Decreased appetite | 18 | 14
Influenza-like illness | 18 | 16
Insomniaa | 16 | 15
Asthenia | 16 | 13
Cough | 15 | 12
Pruritus | 15 | 13
Chills | 14 | 9
Myalgia | 12 | 10
Alopecia | 10 | 6
Peripheral edema | 10 | 5
a Includes PTs of insomnia, initial insomnia, and poor quality sleep.

Rash was reported in 9% and 7% of patients receiving eltrombopag and placebo, respectively.

In the two controlled clinical trials in patients with chronic hepatitis C, hyperbilirubinemia was reported in 8% of patients receiving eltrombopag compared with 3% for placebo. Total bilirubin greater than or equal to 1.5 x ULN was reported in 76% and 50% of patients receiving eltrombopag and placebo, respectively. ALT or AST greater than or equal to 3 x ULN was reported in 34% and 38% of patients for eltrombopag and placebo, respectively.

In the two controlled clinical trials in patients with chronic hepatitis C, cataracts developed or worsened in 8% of patients treated with eltrombopag and 5% of patients treated with placebo.

The safety of eltrombopag was also assessed in all patients treated with eltrombopag in the two controlled trials, including patients who initially received eltrombopag in the pre-antiviral treatment phase of the trial and were later randomized to the placebo arm (N = 1520 eltrombopag-treated patients). Hepatic failure was reported in 0.8% of eltrombopag-treated patients and 0.4% of placebo-treated patients.

Severe Aplastic Anemia:

Refractory Severe Aplastic Anemia

In the single-arm, open-label trial, 43 patients with refractory severe aplastic anemia received eltrombopag. Eleven patients (26%) were treated for greater than 6 months and 7 patients (16%) were treated for greater than 1 year. The most common adverse reactions (greater than or equal to 20%) were nausea, fatigue, cough, diarrhea, and headache.

Table 8. Adverse Reactions (≥ 10%) From One Open-label Trial in Adults with Refractory Severe Aplastic Anemia
Adverse Reaction | Eltrombopag; n = 43; (%)
Nausea | 33
Fatigue | 28
Cough | 23
Diarrhea | 21
Headache | 21
Pain in extremity | 19
Pyrexia | 14
Dizziness | 14
Oropharyngeal pain | 14
Abdominal pain | 12
Muscle spasms | 12
Transaminases increased | 12
Arthralgia | 12
Rhinorrhea | 12

Rash and hyperbilirubinemia were reported in 7% of patients; cataract was reported in 2% of patients.

In this trial, concurrent ALT or AST greater than 3 x ULN with total bilirubin greater than 1.5 x ULN were reported in 5% of patients. Total bilirubin greater than 1.5 x ULN occurred in 14% of patients.

In this trial, patients had bone marrow aspirates evaluated for cytogenetic abnormalities. Eight patients had a new cytogenetic abnormality reported on therapy, including 5 patients who had complex changes in chromosome 7.

6.2 Postmarketing Experience

The following adverse reactions have been identified during post approval use of eltrombopag. Because these reactions are reported voluntarily from a population of uncertain size, it is not always possible to reliably estimate the frequency or establish a causal relationship to drug exposure.

Skin and Subcutaneous Tissue Disorders: Skin discoloration, including hyperpigmentation and skin yellowing.

7 DRUG INTERACTIONS

7.1 Polyvalent Cations (Chelation)

Eltrombopag chelates polyvalent cations (such as iron, calcium, aluminum, magnesium, selenium, and zinc) in foods, mineral supplements, and antacids.

Take ALVAIZ at least 2 hours before or 4 hours after any medications or products containing polyvalent cations, such as antacids, dairy products, and mineral supplements to avoid significant reduction in absorption of ALVAIZ due to chelation [see Dosage and Administration (2.4), Clinical Pharmacology (12.3)].

7.2 Transporters

Use caution when concomitantly administering ALVAIZ and drugs that are substrates of OATP1B1 (e.g., atorvastatin, bosentan, ezetimibe, fluvastatin, glyburide, olmesartan, pitavastatin, pravastatin, rosuvastatin, repaglinide, rifampin, simvastatin acid, SN-38 [active metabolite of irinotecan], valsartan) or breast cancer resistance protein (BCRP) (e.g., imatinib, irinotecan, lapatinib, methotrexate, mitoxantrone, rosuvastatin, sulfasalazine, topotecan). Monitor patients closely for signs and symptoms of excessive exposure to the drugs that are substrates of OATP1B1 or BCRP and consider reduction of the dose of these drugs, if appropriate. In clinical trials with eltrombopag, a dose reduction of rosuvastatin by 50% was recommended.

7.3 Protease Inhibitors

HIV Protease Inhibitors: No dose adjustment is recommended when ALVAIZ is coadministered with lopinavir/ritonavir (LPV/RTV). Drug interactions with other HIV protease inhibitors have not been evaluated.

Hepatitis C Virus Protease Inhibitors: No dose adjustments are recommended when ALVAIZ is coadministered with boceprevir or telaprevir. Drug interactions with other hepatitis C virus (HCV) protease inhibitors have not been evaluated.

7.4 Peginterferon Alfa-2a/b Therapy

No dose adjustments are recommended when ALVAIZ is coadministered with peginterferon alfa-2a (PEGASYS®) or -2b (PEGINTRON®).

7.5 Interference with Clinical Laboratory Tests

Eltrombopag (ALVAIZ) is highly colored and can cause patient sample discoloration, which is reported to interfere with some clinical laboratory tests, including, but not limited to bilirubin and creatinine.

Bilirubin Testing: Eltrombopag can cause both positive and negative interference with bilirubin assays. If the laboratory results for bilirubin are inconsistent with clinical observations, further evaluation of liver function should be performed to clarify the clinical status of the patient. Evaluating contemporaneous aminotransferase values (AST, ALT) may help determine the validity of normal total bilirubin levels in the presence of clinical jaundice.

Creatinine Testing: Eltrombopag can cause positive interference with creatinine measurements, leading to falsely elevated creatinine levels. In the event of an unexpected serum creatinine test result, further evaluation of renal function should be performed. Blood urea should be evaluated if serum creatinine is unexpectedly high.

Communicate to the lab conducting testing if the patient is taking ALVAIZ. Re-testing using other methods may also help in determining the validity of the test results.

8 USE IN SPECIFIC POPULATIONS

8.1 Pregnancy

Risk Summary

Available data from a small number of published case reports and postmarketing experience with eltrombopag use in pregnant women are insufficient to assess any drug-associated risks for major birth defects, miscarriage, or adverse maternal or fetal outcomes. In animal reproduction and developmental toxicity studies, oral administration of eltrombopag to pregnant rats during organogenesis resulted in embryolethality and reduced fetal weights at maternally toxic doses. These effects were observed at doses resulting in exposures that were six times the human clinical exposure based on area under the curve (AUC) in patients with persistent or chronic ITP at 75 mg/day, and three times the AUC in patients with chronic hepatitis C at 100 mg/day (see Data).

The estimated background risk of major birth defects and miscarriage for the indicated population is unknown. All pregnancies have a background risk of birth defect, loss, or other adverse outcomes. In the U.S. general population, the estimated background risk of major birth defects and of miscarriage in clinically recognized pregnancies is 2% to 4% and 15% to 20%, respectively.

Data

Animal Data

In an early embryonic development study, female rats received oral eltrombopag at doses of 10, 20, or 60 mg/kg/day (0.8, 2, and 6 times, respectively, the human clinical exposure based on AUC in patients with ITP at 75 mg/day and 0.3, 1, and 3 times, respectively, the human clinical exposure based on AUC in patients with chronic hepatitis C at 100 mg/day). Increased pre- and post-implantation loss and reduced fetal weight were observed at the highest dose which also caused maternal toxicity.

In an embryo-fetal development study eltrombopag was administered orally to pregnant rats during the period of organogenesis at doses of 10, 20, or 60 mg/kg/day (0.8, 2, and 6 times, respectively, the human clinical exposure based on AUC in patients with ITP at 75 mg/day and 0.3, 1, and 3 times, respectively, the human clinical exposure based on AUC in patients with chronic hepatitis C at 100 mg/day). Decreased fetal weights (6% to 7%) and a slight increase in the presence of cervical ribs were observed at the highest dose which also caused maternal toxicity. However, no evidence of major structural malformations was observed.

In an embryo-fetal development study eltrombopag was administered orally to pregnant rabbits during the period of organogenesis at doses of 30, 80, or 150 mg/kg/day (0.04, 0.3, and 0.5 times, respectively, the human clinical exposure based on AUC in patients with ITP at 75 mg/day and 0.02, 0.1, and 0.3 times, respectively, the human clinical exposure based on AUC in patients with chronic hepatitis C at 100 mg/day). No evidence of fetotoxicity, embryolethality, or teratogenicity was observed.

In a pre- and post-natal developmental toxicity study in pregnant rats (F0), oral eltrombopag was administered from gestation Day 6 through lactation Day 20. No adverse effects on maternal reproductive function or on the development of the offspring (F1) were observed at doses up to 20 mg/kg/day (2 times the human clinical exposure based on AUC in patients with ITP at 75 mg/day and similar to the human clinical exposure based on AUC in patients with chronic hepatitis C at 100 mg/day). Eltrombopag was detected in the plasma of offspring (F1). The plasma concentrations in pups increased with dose following administration of drug to the F0 dams.

8.2 Lactation

Risk Summary

There are no data regarding the presence of eltrombopag or its metabolites in human milk, the effects on the breastfed child, or the effects on milk production. However, eltrombopag was detected in the pups of lactating rats 10 days postpartum suggesting the potential for transfer during lactation. Due to the potential for serious adverse reactions in a breastfed child from eltrombopag, breastfeeding is not recommended during treatment.

8.3 Females and Males of Reproductive Potential

Contraception

Based on animal reproduction studies, eltrombopag can cause fetal harm when administered to a pregnant woman. Sexually-active females of reproductive potential should use effective contraception (methods that result in less than 1% pregnancy rates) when using ALVAIZ during treatment and for at least 7 days after stopping treatment with ALVAIZ.

8.4 Pediatric Use

The safety and effectiveness of ALVAIZ have been established in pediatric patients 6 years and older with persistent or chronic ITP.

The safety and effectiveness of eltrombopag in pediatric patients 6 years and older with persistent or chronic ITP were evaluated in two double-blind, placebo-controlled trials [see Adverse Reactions (6.1), Clinical Studies (14.1)]. The pharmacokinetics of eltrombopag have been established in 130 pediatric patients 6 years and older with ITP dosed once daily [see Clinical Pharmacology (12.3)]. See Dosage and Administration (2.1) for dosing recommendations for pediatric patients 6 years and older.

The safety and effectiveness of ALVAIZ have not been established in pediatric patients less than 6 years of age with persistent or chronic ITP. Pediatric patients must be able to swallow ALVAIZ tablets whole [see Dosage and Administration (2.5)].

The safety and effectiveness in pediatric patients with thrombocytopenia associated with chronic hepatitis C and refractory severe aplastic anemia have not been established.

8.5 Geriatric Use

Of the 106 patients in two randomized clinical trials of eltrombopag 50 mg in persistent or chronic ITP, 22% were 65 years of age and over, while 9% were 75 years of age and over. Of the 1439 patients in two randomized clinical trials of eltrombopag in patients with chronic hepatitis C and thrombocytopenia, 7% were 65 years of age and over, while < 1% were 75 years of age and over. Of the 196 patients who received eltrombopag for the treatment of severe aplastic anemia, 18% were 65 years of age and over, while 3% were 75 years of age and over. No overall differences in safety or effectiveness were observed between these patients and younger patients.

8.6 Hepatic Impairment

Patients with Persistent or Chronic ITP and Severe Aplastic Anemia

Reduce the initial dose of eltrombopag in patients with persistent or chronic ITP (adult and pediatric patients 6 years and older only) or refractory severe aplastic anemia who also have hepatic impairment (Child-Pugh Class A, B, C) [see Dosage and Administration (2.1, 2.3), Warnings and Precautions (5.2), Clinical Pharmacology (12.3)].

In a clinical trial in patients with severe aplastic anemia who had not received prior definitive immunosuppressive therapy, patients with baseline ALT or AST > 5 x ULN were ineligible to participate [see Dosage and Administration (2.3), Warnings and Precautions (5.2), Clinical Pharmacology (12.3)].

Patients with Chronic Hepatitis C

No dosage adjustment is recommended in patients with chronic hepatitis C and hepatic impairment [see Clinical Pharmacology (12.3)].

8.7 Ethnicity

Reduce the initial dose of ALVAIZ for patients of East- /Southeast-Asian ancestry with ITP (adult and pediatric patients 6 years and older only) or adults with severe aplastic anemia [see Dosage and Administration (2.1, 2.3), Clinical Pharmacology (12.3)]. No reduction in the initial dose of ALVAIZ is recommended in patients of East-/Southeast-Asian ancestry with chronic hepatitis C [see Clinical Pharmacology (12.3)].

10 OVERDOSAGE

In the event of overdose, platelet counts may increase excessively and result in thrombotic/thromboembolic complications.

In one report, a subject who ingested 5000 mg of eltrombopag had a platelet count increase to a maximum of 929 x 10^9/L at 13 days following the ingestion. The patient also experienced rash, bradycardia, ALT/AST elevations, and fatigue. The patient was treated with gastric lavage, oral lactulose, intravenous fluids, omeprazole, atropine, furosemide, calcium, dexamethasone, and plasmapheresis; however, the abnormal platelet count and liver test abnormalities persisted for 3 weeks. After 2 months’ follow-up, all events had resolved without sequelae.

In case of an overdose, consider oral administration of a metal cation-containing preparation, such as calcium, aluminum, or magnesium preparations to chelate eltrombopag and thus limit absorption. Closely monitor platelet counts. Reinitiate treatment with eltrombopag in accordance with dosing and administration recommendations [see Dosage and Administration (2.1, 2.2)]. Consider contacting the Poison Help line (1-800-222-1222) or a medical toxicologist for additional overdose management recommendations.

11 DESCRIPTION

ALVAIZ (eltrombopag) tablets contain eltrombopag choline, a small molecule thrombopoietin (TPO) receptor agonist for oral administration.

Eltrombopag choline is a biphenyl hydrazone. The chemical name for eltrombopag choline is (Z)-3’-(2-(1-(3,4-dimethylphenyl)-3-methyl-5-oxo-1h-Pyrazol-4(5h)-ylidene)hydrazinyl)-2’-hydroxybiphenyl-3-carboxylic acid -choline (1:1). It has the molecular formula C30H35N5O5. The molecular weight is 545.63 g/mol for eltrombopag choline and 442.47 g/mol for eltrombopag free acid.

Eltrombopag choline has the following structural formula:

Eltrombopag choline is practically insoluble in aqueous buffer across a pH range of 1.2 to 6.8.

ALVAIZ (eltrombopag) tablets contain 9 mg, 18 mg, 36 mg, or 54 mg of eltrombopag, supplied as 11.1 mg, 22.2 mg, 44.4 mg, and 66.6 mg of eltrombopag choline, respectively. The inactive ingredients of ALVAIZ tablets are:

Tablet Core: anhydrous lactose, copovidone, croscarmellose sodium, edetate disodium dihydrate, magnesium stearate, poloxamer 188, polyethylene glycol 4000, povidone K12, silicified microcrystalline cellulose, and silicon dioxide.

Coating:

Strength
9 mg: | FD&C Blue No. 1 aluminum lake, polyethylene glycol 3350, polyvinyl alcohol, talc, and titanium dioxide.
18 mg: | Hypromellose 2910, polyethylene glycol 4000, talc, and titanium dioxide.
36 mg: | Iron oxide red, iron oxide yellow, polyethylene glycol 3350, polyvinyl alcohol, talc, and titanium dioxide.
54 mg: | FD&C Red #40 aluminum lake, hypromellose 2910, iron oxide yellow, polyethylene glycol 400, and titanium dioxide.

12 CLINICAL PHARMACOLOGY

12.1 Mechanism of Action

Eltrombopag is a TPO-receptor agonist that interacts with the transmembrane domain of the human TPO-receptor (also known as cMpl) and initiates signaling cascades that induce proliferation and differentiation of megakaryocytes leading to increased platelet production.

12.2 Pharmacodynamics

In clinical trials, treatment with eltrombopag resulted in dose-dependent increases in platelet counts following repeated (daily) dosing. The increase in platelet counts reached a maximum approximately two weeks after the initiation of dosing, and returned to baseline within approximately two weeks after the last dose of eltrombopag.

Cardiac Electrophysiology

At doses up to 150 mg (the maximum recommended dose) daily for 5 days, eltrombopag did not prolong the QT/QTc interval to any relevant extent.

12.3 Pharmacokinetics

Eltrombopag demonstrated a dose-proportional increase in exposure between doses of 50 to 150 mg/day in healthy adult subjects. Eltrombopag AUC was approximately 1.7-fold higher in patients with persistent or chronic ITP and approximately 2.8-fold higher in patients with HCV compared to healthy subjects. Steady-state was achieved after approximately 1 week of once daily treatment, with geometric mean accumulation ratio of 1.56 (90% confidence interval 1.20, 1.63) at 75 mg/day. Eltrombopag AUC was approximately 3.2-fold higher in patients with definitive immunosuppressive therapy-naïve severe aplastic anemia compared to healthy subjects suggesting higher relative exposure compared to healthy subjects or patients with ITP and similar exposure compared to patients with chronic hepatitis C.

Absorption

Eltrombopag is absorbed with a peak concentration occurring 1.5 to 5.5 hours after oral administration under fasting conditions and 1.0 to 8.0 hours after oral administration under fed conditions (high-fat, high-calorie meal).

Effect of Food

Administration of eltrombopag after a high fat, high calorie meal decreased AUCinf by approximately 36% and Cmax by approximately 39%, and delayed Tmax by 0.5 hours as compared to fasted conditions.

A meal low in calcium (≤ 50 mg calcium) did not significantly impact plasma eltrombopag exposure, regardless of calorie and fat content.

Distribution

The concentration of eltrombopag in blood cells is approximately 50% to 79% of plasma concentrations based on a radiolabel study. In vitro studies suggest that eltrombopag is highly bound to human plasma proteins (greater than 99%). Eltrombopag is a substrate of BCRP, but is not a substrate for P-glycoprotein (P-gp) or OATP1B1.

Elimination

The plasma elimination half-life of eltrombopag is approximately 21 to 32 hours in healthy subjects and 26 to 35 hours in patients with ITP.

Metabolism: Absorbed eltrombopag is extensively metabolized, predominantly through pathways, including cleavage, oxidation, and conjugation with glucuronic acid, glutathione, or cysteine. In vitro studies suggest that CYP1A2 and CYP2C8 are responsible for the oxidative metabolism of eltrombopag. UGT1A1 and UGT1A3 are responsible for the glucuronidation of eltrombopag.

Excretion: The predominant route of eltrombopag excretion is via feces (59%), and 31% of the dose is found in the urine. Unchanged eltrombopag in feces accounts for approximately 20% of the dose; unchanged eltrombopag is not detectable in urine.

Specific Populations

Ethnicity

Eltrombopag concentrations in East-/Southeast-Asian ancestry patients with ITP or chronic hepatitis C, were 50% to 55% higher compared with non-Asian subjects [see Dosage and Administration (2.1, 2.3)].

Eltrombopag exposure in healthy African-American subjects was approximately 40% higher than that observed in Caucasian subjects in one clinical pharmacology trial and similar in three other clinical pharmacology trials. The effect of African-American ethnicity on exposure and related safety and efficacy of eltrombopag has not been established.

Hepatic Impairment

Following a single dose of eltrombopag, plasma eltrombopag AUC0-INF was 41% higher in patients with mild hepatic impairment (Child-Pugh Class A) compared with subjects with normal hepatic function.

Plasma eltrombopag AUC0-INF was approximately 2-fold higher in patients with moderate (Child-Pugh Class B) and severe hepatic impairment (Child-Pugh Class C) compared with subjects with normal hepatic function. The half-life of eltrombopag was prolonged 2-fold in these patients. This clinical trial did not evaluate protein-binding effects.

Chronic Liver Disease

Following repeat doses of eltrombopag in patients with thrombocytopenia and with chronic liver disease, mild hepatic impairment resulted in an 87% to 110% higher plasma eltrombopag AUC(0-τ) and moderate hepatic impairment resulted in approximately 141% to 240% higher plasma eltrombopag AUC(0-τ) values compared with patients with normal hepatic function. The half-life of eltrombopag was prolonged 3-fold in patients with mild hepatic impairment and 4-fold in patients with moderate hepatic impairment. This clinical trial did not evaluate protein-binding effects.

Chronic Hepatitis C

Patients with chronic hepatitis C treated with eltrombopag had higher plasma AUC(0-τ) values as compared with healthy subjects, and AUC(0-τ) increased with increasing Child-Pugh score. Patients with chronic hepatitis C and mild hepatic impairment had approximately 100% to 144% higher plasma AUC(0-τ) compared with healthy subjects. This clinical trial did not evaluate protein-binding effects.

Renal Impairment

Following a single dose of eltrombopag, the average total plasma eltrombopag AUC0-INF was
32% to 36% lower in subjects with mild (estimated creatinine clearance (CLCr) by Cockcroft-Gault equation: 50 to 80 mL/min), to moderate (CLCr of 30 to 49 mL/min) renal impairment and 60% lower in subjects with severe (CLCr less than 30 mL/min) renal impairment compared with healthy subjects. The effect of renal impairment on unbound (active) eltrombopag exposure has not been assessed.

Pediatric Patients

The pharmacokinetics of eltrombopag have been evaluated in 168 pediatric patients 1 year and older with ITP dosed once daily in two trials. Plasma eltrombopag apparent clearance following oral administration (CL/F) increased with increasing body weight. East-/Southeast-Asian pediatric patients with ITP had approximately 43% higher plasma eltrombopag AUC(0-τ) values as compared with non-Asian patients.

Plasma eltrombopag AUC(0-τ) and Cmax in pediatric patients aged 12 to 17 years was similar to that observed in adults. The pharmacokinetic parameters of eltrombopag in pediatric patients with ITP are shown in Table 9.

Table 9. Geometric Mean (95% CI) Steady-state Plasma Eltrombopag Pharmacokinetic Parametersa in Patients with ITP (Normalized to a Once-daily 50-mg Dose, Equivalent to ALVAIZ 36 mg Once-daily)
Age | Cmaxb; (mcg/mL) | AUC(0-τ)b; (mcg·hr/mL)
Adults (n = 108) | 7.03; (6.44, 7.68) | 101; (91.4, 113)
12 to 17 years (n = 62) | 6.80; (6.17, 7.50) | 103; (91.1, 116)
6 to 11 years (n = 68) | 10.3; (9.42, 11.2) | 153; (137, 170)
aPK parameters presented as geometric mean (95% CI).
bBased on population PK post-hoc estimates.

Drug Interaction Studies

Clinical Studies

Effect of Drugs on Eltrombopag

Effect of Polyvalent Cation-containing Antacids on Eltrombopag:

The coadministration of a single dose of eltrombopag with a polyvalent cation-containing antacid (1,524 mg aluminum hydroxide, 1,425 mg magnesium carbonate, and sodium alginate) decreased plasma eltrombopag AUC0-INF and Cmax by approximately 70%. The contribution of sodium alginate to this interaction is not known.

Effect of HIV Protease Inhibitors on Eltrombopag:

The coadministration of repeat-dose lopinavir 400 mg/ritonavir 100 mg (twice daily) with a single dose of eltrombopag decreased plasma eltrombopag AUC0-INF by 17%.

Effect of HCV Protease Inhibitors on Eltrombopag:

The coadministration of repeat-dose telaprevir (750 mg every 8 hours) or boceprevir (800 mg every 8 hours) with a single dose of eltrombopag to healthy adult subjects in a clinical trial did not alter plasma eltrombopag AUC0-INF or Cmax to a significant extent.

Effect of Cyclosporine on Eltrombopag:

The coadministration of a single dose of eltrombopag with a single dose of an OATP and BCRP inhibitor cyclosporine (200 mg or 600 mg) decreased plasma eltrombopag AUC0-INF by 18% to 24% and Cmax by 25% to 39%.

Effect of Pegylated Interferon alfa-2a + Ribavirin and Pegylated Interferon alfa-2b + Ribavirin on Eltrombopag:

The presence of pegylated interferon alfa + ribavirin therapy did not significantly affect the clearance of eltrombopag.

Effect of Eltrombopag on Other Drugs

Effect of Eltrombopag on Cytochrome P450 Enzymes Substrates:

The coadministration of multiple doses of eltrombopag (once daily for 7 days) did not result in the inhibition or induction of the metabolism of a combination of probe substrates for CYP1A2 (caffeine), CYP2C19 (omeprazole), CYP2C9 (flurbiprofen), or CYP3A4 (midazolam) in humans.

Effect of Eltrombopag on Rosuvastatin:

The coadministration of multiple doses of eltrombopag (once daily for 5 days) with a single dose of rosuvastatin (OATP1B1 and BCRP substrate; 10 mg) increased plasma rosuvastatin AUC0-INF by 55% and Cmax by 103%.

Effect of Eltrombopag on HCV Protease Inhibitors:

The coadministration of repeat-dose telaprevir (750 mg every 8 hours) or boceprevir (800 mg every 8 hours) with a single dose of eltrombopag to healthy adult subjects in a clinical trial did not alter plasma telaprevir or boceprevir AUC0-INF or Cmax to a significant extent.

In vitro Studies

Eltrombopag Effect on Metabolic Enzymes

Eltrombopag has demonstrated the potential to inhibit CYP2C8, CYP2C9, UGT1A1, UGT1A3, UGT1A4, UGT1A6, UGT1A9, UGT2B7, and UGT2B15.

Eltrombopag Effect on Transporters

Eltrombopag has demonstrated the potential to inhibit OATP1B1 and BCRP.

13 NONCLINICAL TOXICOLOGY

13.1 Carcinogenesis, Mutagenesis, Impairment of Fertility

Eltrombopag does not stimulate platelet production in rats, mice, or dogs because of unique TPO receptor specificity. Data from these animals do not fully model effects in humans.

Eltrombopag was not carcinogenic in mice at doses up to 75 mg/kg/day or in rats at doses up to 40 mg/kg/day (exposures up to 4 times the human clinical exposure based on AUC in patients with ITP at 75 mg/day and 2 times the human clinical exposure based on AUC in patients with chronic hepatitis C at 100 mg/day).

Eltrombopag was not mutagenic or clastogenic in a bacterial mutation assay or in two in vivo assays in rats (micronucleus and unscheduled DNA synthesis, 10 times the human clinical exposure based on Cmax in patients with ITP at 75 mg/day and 7 times the human clinical exposure based on Cmax in patients with chronic hepatitis C at 100 mg/day). In the in vitro mouse lymphoma assay, eltrombopag was marginally positive (less than 3-fold increase in mutation frequency).

Eltrombopag did not affect female fertility in rats at doses up to 20 mg/kg/day (2 times the human clinical exposure based on AUC in patients with ITP at 75 mg/day and similar to the human clinical exposure based on AUC in patients with chronic hepatitis C at 100 mg/day). Eltrombopag did not affect male fertility in rats at doses up to 40 mg/kg/day, the highest dose tested (3 times the human clinical exposure based on AUC in patients with ITP at 75 mg/day and 2 times the human clinical exposure based on AUC in patients with chronic hepatitis C at 100 mg/day).

13.2 Animal Toxicology and/or Pharmacology

Treatment-related cataracts were detected in rodents in a dose- and time-dependent manner. At greater than or equal to 6 times the human clinical exposure based on AUC in patients with ITP at 75 mg/day and 3 times the human clinical exposure based on AUC in patients with chronic hepatitis C at 100 mg/day, cataracts were observed in mice after 6 weeks and in rats after 28 weeks of dosing. At greater than or equal to 4 times the human clinical exposure based on AUC in patients with ITP at 75 mg/day and 2 times the human clinical exposure based on AUC in patients with chronic hepatitis C at 100 mg/day, cataracts were observed in mice after 13 weeks and in rats after 39 weeks of dosing [see Warnings and Precautions (5.5)].

Renal tubular toxicity was observed in studies up to 14 days in duration in mice and rats at exposures that were generally associated with morbidity and mortality. Tubular toxicity was also observed in a 2-year oral carcinogenicity study in mice at doses of 25, 75, and 150 mg/kg/day. The exposure at the lowest dose was 1.2 times the human clinical exposure based on AUC in patients with ITP at 75 mg/day and 0.6 times the human clinical exposure based on AUC in patients with chronic hepatitis C at 100 mg/day. No similar effects were observed in mice after 13 weeks at exposures greater than those associated with renal changes in the 2-year study, suggesting that this effect is both dose- and time-dependent.

14 CLINICAL STUDIES

The effectiveness of ALVAIZ has been established based on adequate and well-controlled studies of eltrombopag olamine in adult and pediatric patients 6 years and older with persistent or chronic ITP, adult patients with chronic hepatitis C-associated thrombocytopenia, and adult patients with refractory severe aplastic anemia. Below is a display of the efficacy information for eltrombopag olamine in these adequate and well-controlled studies.

14.1 Persistent or Chronic ITP

Adults: The efficacy and safety of eltrombopag in adult patients with persistent or chronic ITP were evaluated in three randomized, double-blind, placebo-controlled trials and in an open-label extension trial.

In Study TRA100773B and Study TRA100773A (referred to as Study 773B and Study 773A, respectively [NCT00102739]), patients who had completed at least one prior ITP therapy and who had a platelet count less than 30 x 10^9/L were randomized to receive either eltrombopag or placebo daily for up to 6 weeks, followed by 6 weeks off therapy. During the trials, eltrombopag or placebo was discontinued if the platelet count exceeded 200 x 10^9/L.

The median age of the patients was 50 years and 60% were female. Approximately 70% of the patients had received at least 2 prior ITP therapies (predominantly corticosteroids, immunoglobulins, rituximab, cytotoxic therapies, danazol, and azathioprine) and 40% of the patients had undergone splenectomy. The median baseline platelet counts (approximately 18 x 10^9/L) were similar among all treatment groups.

Study 773B randomized 114 patients (2:1) to eltrombopag 50 mg or placebo. Of 60 patients with documented time since diagnosis, approximately 17% met the definition of persistent ITP with time since diagnosis of 3 to 12 months. Study 773A randomized 117 patients (1:1:1:1) among placebo or 1 of 3 dose regimens of eltrombopag , 30 mg, 50 mg, or 75 mg each administered daily. Of 51 patients with documented time since diagnosis, approximately 14% met the definition of persistent ITP.

The efficacy of eltrombopag in this trial was evaluated by response rate, defined as a shift from a baseline platelet count of less than 30 x 10^9/L to greater than or equal to 50 x 10^9/L at any time during the treatment period (Table 10).

Table 10. Studies 773B and 773A: Platelet Count Response (≥ 50 x 10^9/L) Rates in Adults with Persistent or Chronic Immune Thrombocytopenia
Study | Eltrombopag 50 mg Daily | Placebo
773B | 43/73 (59%)a | 6/37 (16%)
773A | 19/27 (70%)a | 3/27 (11%)
a p-value < 0.001 for eltrombopag versus placebo.

The platelet count response to eltrombopag was similar among patients who had or had not undergone splenectomy. In general, increases in platelet counts were detected 1 week following initiation of eltrombopag and the maximum response was observed after 2 weeks of therapy. In the placebo and 50-mg dose groups of eltrombopag, the trial drug was discontinued due to an increase in platelet counts to greater than 200 x 10^9/L in 3% and 27% of the patients, respectively. The median duration of treatment with the 50-mg dose of eltrombopag was 43 days in Study 773B and 42 days in Study 773A.

Of 7 patients who underwent hemostatic challenges, additional ITP medications were required in 3 of 3 placebo group patients and 0 of 4 patients treated with eltrombopag. Surgical procedures accounted for most of the hemostatic challenges. Hemorrhage requiring transfusion occurred in one placebo group patient and no patients treated with eltrombopag.

In the RAISE study (NCT00370331), 197 patients were randomized (2:1) to receive either eltrombopag 50 mg once daily (n = 135) or placebo (n = 62) for 6 months, during which time the dose of eltrombopag could be adjusted based on individual platelet counts. Of 145 patients with documented time since diagnosis, 19% met the definition of persistent ITP. Patients were allowed to taper or discontinue concomitant ITP medications after being treated with eltrombopag for 6 weeks. Patients were permitted to receive rescue treatments at any time during the trial as clinically indicated.

The median ages of the patients treated with eltrombopag and placebo were 47 years and 52.5 years, respectively. Approximately half of the patients treated with eltrombopag and placebo (47% and 50%, respectively) were receiving concomitant ITP medication (predominantly corticosteroids) at randomization and had baseline platelet counts less than or equal to 15 x 10^9/L (50% and 48%, respectively). A similar percentage of patients treated with eltrombopag and placebo (37% and 34%, respectively) had a prior splenectomy.

The efficacy of eltrombopag in this trial was evaluated by the odds of achieving a platelet count greater than or equal to 50 x 10^9/L and less than or equal to 400 x 10^9/L for patients receiving eltrombopag relative to placebo and was based on patient response profiles throughout the 6-month treatment period. In 134 patients who completed 26 weeks of treatment, a sustained platelet response (platelet count greater than or equal to 50 x 10^9/L and less than or equal to 400 x 10^9/L for 6 out of the last 8 weeks of the 26-week treatment period in the absence of rescue medication at any time) was achieved by 60% of patients treated with eltrombopag, compared with 10% of patients treated with placebo (splenectomized patients: eltrombopag 51%, placebo 8%; non-splenectomized patients: eltrombopag 66%, placebo 11%). The proportion of responders in the group of patients treated with eltrombopag was between 37% and 56% compared with 7% and 19% in the placebo treatment group for all on-therapy visits. Patients treated with eltrombopag were significantly more likely to achieve a platelet count between 50 x 10^9/L and 400 x 10^9/L during the entire 6-month treatment period compared with those patients treated with placebo.

Outcomes of treatment are presented in Table 11 for all patients enrolled in the trial.

Table 11. RAISE: Outcomes of Treatment in Adults with Persistent or Chronic Immune Thrombocytopenia
Outcome | Eltrombopag; n = 135 | Placebo; n = 62
Mean number of weeks with platelet counts ≥ 50 x 10^9/L | 11.3 | 2.4
Requiring rescue therapy, n (%) | 24 (18) | 25 (40)

Among 94 patients receiving other ITP therapy at baseline, 37 (59%) of 63 patients treated with eltrombopag and 10 (32%) of 31 patients in the placebo group discontinued concomitant therapy at some time during the trial.

In the EXTEND study (NCT00351468), patients who completed any prior clinical trial with eltrombopag were enrolled in an open-label, single-arm trial in which attempts were made to decrease the dose or eliminate the need for any concomitant ITP medications. Eltrombopag was administered to 302 patients in EXTEND; 218 patients completed 1 year, 180 patients completed 2 years, 107 patients completed 3 years, 75 patients completed 4 years, 34 patients completed 5 years, and 18 patients completed 6 years of therapy. The median baseline platelet count was 19 x 10^9/L prior to administration of eltrombopag. Median platelet counts at 1, 2, 3, 4, 5, 6, and 7 years on study were 85 x 10^9/L, 85 x 10^9/L, 105 x 10^9/L, 64 x 10^9/L, 75 x 10^9/L, 119 x 10^9/L, and 76 x 10^9/L, respectively.

Pediatric Patients: The efficacy and safety of eltrombopag in pediatric patients 1 year and older with persistent or chronic ITP were evaluated in two double-blind, placebo-controlled trials. ALVAIZ is not indicated for pediatric patients less than 6 years of age with persistent or chronic ITP. The trials differed in time since ITP diagnosis: at least 6 months versus at least 12 months. During the trials, doses could be increased every 2 weeks to a maximum of 75 mg once daily. The dose of eltrombopag was reduced if the platelet count exceeded 200 x 10^9/L and interrupted and reduced if it exceeded 400 x 10^9/L.

In the PETIT2 study (NCT01520909), patients refractory or relapsed to at least one prior ITP therapy with a platelet count less than 30 x 10^9/L (n = 92) were stratified by age and randomized (2:1) to eltrombopag (n = 63) or placebo (n = 29). The starting dose for patients aged 6 to 17 years was 50 mg once daily for those at least 27 kg and 37.5 mg once daily for those less than 27 kg, administered as oral tablets. A reduced dose of 25 mg once daily was used for East-/Southeast-Asian patients aged 6 to 17 years regardless of weight.

The 13-week, randomized, double-blind period was followed by a 24-week, open-label period where patients from both arms were eligible to receive eltrombopag.

The median age of the patients was 9 years and 48% were female. Approximately 62% of patients had a baseline platelet count less than or equal to 15 x 10^9/L, a characteristic that was similar between treatment arms. The percentage of patients with at least 2 prior ITP therapies (predominantly corticosteroids and immunoglobulins) was 73% in the group treated with eltrombopag and 90% in the group treated with placebo. Four patients in the group treated with eltrombopag had undergone splenectomy.

The efficacy of eltrombopag in this trial was evaluated by the proportion of subjects on eltrombopag achieving platelet counts ≥ 50 x 10^9/L (in the absence of rescue therapy) for at least 6 out of 8 weeks between Weeks 5 to 12 of the randomized, double-blind period (Table 12).

Table 12. PETIT2: Platelet Count Response (≥ 50 x 10^9/L Without Rescue) for 6 out of 8 Weeks (between Weeks 5 to 12) Overall and by Age Cohort in Pediatric Patients 1 Year and Older with Chronic Immune Thrombocytopenia
Age Cohort | Eltrombopag | Placebo
Overall; 12 to 17 years; 6 to 11 years; 1 to 5 years | 26/63 (41%)a; 10/24 (42%); 11/25 (44%); 5/14 (36%) | 1/29 (3%); 1/10 (10%); 0/13 (0%); 0/6 (0%)
a p-value = < 0.001 for eltrombopag versus placebo.

More pediatric patients treated with eltrombopag (75%) compared with placebo (21%) had at least one platelet count greater than or equal to 50 x 10^9/L during the first 12 weeks of randomized treatment in absence of rescue therapy. Fewer pediatric patients treated with eltrombopag required rescue treatment during the randomized, double-blind period compared with placebo-treated patients (19% [12/63] versus 24% [7/29]). In the patients who achieved a platelet response (≥ 50 x 10^9/L without rescue) for 6 out of 8 weeks (between weeks 5 to 12), 62% (16/26) had an initial response in the first 2 weeks after starting eltrombopag.

Patients were permitted to reduce or discontinue baseline ITP therapy only during the open-label phase of the trial. Among 15 patients receiving other ITP therapy at baseline, 53% (8/15) reduced (n = 1) or discontinued (n = 7) concomitant therapy, mainly corticosteroids, without needing rescue therapy.

In the PETIT study (NCT00908037), patients refractory or relapsed to at least one prior ITP therapy with a platelet count less than 30 x 10^9/L (n = 67) were stratified by age and randomized (2:1) to eltrombopag (n = 45) or placebo (n = 22). Approximately 15% of patients met the definition of persistent ITP. The starting dose for patients aged 12 to 17 years was 37.5 mg once daily regardless of weight or race. The starting dose for patients aged 6 to 11 years was 50 mg once daily for those greater than or equal to 27 kg and 25 mg once daily for those less than 27 kg, administered as oral tablets. Reduced doses of 25 mg (for those greater than or equal to 27 kg) and 12.5 mg (for those less than 27 kg), each once daily, were used for East-/Southeast-Asian patients in this age range.

The 7-week, randomized, double-blind period was followed by an open-label period of up to 24 weeks where patients from both arms were eligible to receive eltrombopag.

The median age of the patients was 10 years and 60% were female. Approximately 51% of patients had a baseline platelet count less than or equal to 15 x 10^9/L. The percentage of patients with at least 2 prior ITP therapies (predominantly corticosteroids and immunoglobulins) was 84% in the group treated with eltrombopag and 86% in the group treated with placebo. Five patients in the group treated with eltrombopag had undergone splenectomy.

The efficacy of eltrombopag in this trial was evaluated by the proportion of patients achieving platelet counts greater than or equal to 50 x 10^9/L (in absence of rescue therapy) at least once between Weeks 1 and 6 of the randomized, double-blind period (Table 13). Platelet response to eltrombopag was consistent across the age cohorts.

Table 13. PETIT: Platelet Count Response (≥ 50 x 10^9/L Without Rescue) Rates in Pediatric Patients 1 Year and Older with Persistent or Chronic Immune Thrombocytopenia
Age Cohort | Eltrombopag | Placebo
Overall | 28/45 (62%)a | 7/22 (32%)
12 to 17 years | 10/16 (62%) | 0/8 (0%)
6 to 11 years | 12/19 (63%) | 3/9 (33%)
a p-value = 0.011 for eltrombopag versus placebo.

Fewer pediatric patients treated with eltrombopag required rescue treatment during the randomized, double-blind period compared with placebo-treated patients (13% [6/45] versus 50% [11/22]).

Patients were permitted to reduce or discontinue baseline ITP therapy only during the open-label phase of the trial. Among 13 patients receiving other ITP therapy at baseline, 46% (6/13) reduced (n = 3) or discontinued (n = 3) concomitant therapy, mainly corticosteroids, without needing rescue therapy.

14.2 Chronic Hepatitis C-associated Thrombocytopenia

The efficacy and safety of eltrombopag for the treatment of thrombocytopenia in adult patients with chronic hepatitis C were evaluated in two randomized, double-blind, placebo-controlled trials. The ENABLE1 study (NCT00516321) utilized peginterferon alfa-2a (PEGASYS®) plus ribavirin for antiviral treatment and the ENABLE2 study (NCT00529568) utilized peginterferon alfa-2b (PEGINTRON®) plus ribavirin. In both trials, patients with a platelet count of less than 75 x 10^9/L were enrolled and stratified by platelet count, screening HCV RNA, and HCV genotype. Patients were excluded if they had evidence of decompensated liver disease with Child-Pugh score greater than 6 (Class B and C), history of ascites, or hepatic encephalopathy. The median age of the patients in both trials was 52 years, 63% were male, and 74% were Caucasian. Sixty-nine percent of patients had HCV genotypes 1, 4, 6, with the remainder genotypes 2 and 3. Approximately 30% of patients had been previously treated with interferon and ribavirin. The majority of patients (90%) had bridging fibrosis and cirrhosis, as indicated by noninvasive testing. A similar proportion (95%) of patients in both treatment groups had Child-Pugh Class A (score 5 to 6) at baseline. A similar proportion of patients (2%) in both treatment groups had baseline international normalized ratio (INR) greater than 1.7. Median baseline platelet counts (approximately 60 x 10^9/L) were similar in both treatment groups. The trials consisted of 2 phases – a pre-antiviral treatment phase and an antiviral treatment phase. In the pre-antiviral treatment phase, patients received open-label eltrombopag to increase the platelet count to a threshold of greater than or equal to 90 x 10^9/L for ENABLE1 and greater than or equal to 100 x 10^9/L for ENABLE2. Eltrombopag was administered at an initial dose of 25 mg once daily for 2 weeks and increased in 25-mg increments over 2- to 3-week periods to achieve the optimal platelet count to initiate antiviral therapy. The maximal time patients could receive open-label eltrombopag was 9 weeks. If threshold platelet counts were achieved, patients were randomized (2:1) to the same dose of eltrombopag at the end of the pre-treatment phase or to placebo. Eltrombopag was administered in combination with pegylated interferon and ribavirin per their respective prescribing information for up to 48 weeks.

The efficacy of eltrombopag for both trials was evaluated by sustained virologic response (SVR) defined as the percentage of patients with undetectable HCV-RNA at 24 weeks after completion of antiviral treatment. The median time to achieve the target platelet count greater than or equal to 90 x 10^9/L was approximately 2 weeks. Ninety-five percent of patients were able to initiate antiviral therapy.

In both trials, a significantly greater proportion of patients treated with eltrombopag achieved SVR (see Table 14). The improvement in the proportion of patients who achieved SVR was consistent across subgroups based on baseline platelet count (less than 50 x 10^9/L versus greater than or equal to 50 x 10^9/L). In patients with high baseline viral loads (greater than or equal to 800,000), the SVR rate was 18% (82/452) for eltrombopag versus 8% (20/239) for placebo.

Table 14. ENABLE1 and ENABLE2: Sustained Virologic Response (SVR) in Adults With Chronic Hepatitis C
Pre-antiviral Treatment Phase | ENABLE1a |  | ENABLE2b
Pre-antiviral Treatment Phase | n = 715 |  | n = 805
% Patients who achieved target platelet counts and initiated antiviral therapyc | 95% |  | 94%
Antiviral Treatment Phase | Eltrombopag; n = 450; % | Placebo n = 232; % | Eltrombopag n = 506; % | Placebo n = 253; %
Overall SVRd; HCV Genotype 2,3; HCV Genotype 1,4,6 | 23; 35; 18 | 14; 24; 10 | 19; 34; 13 | 13; 25; 7
aEltrombopag given in combination with peginterferon alfa-2a (180 mcg once weekly for 48 weeks for genotypes 1/4/6; 24 weeks for genotype 2 or 3) plus ribavirin (800 to 1,200 mg daily in 2 divided doses orally).
bEltrombopag given in combination with peginterferon alfa-2b (1.5 mcg/kg once weekly for 48 weeks for genotypes 1/4/6; 24 weeks for genotype 2 or 3) plus ribavirin (800 to 1,400 mg daily in 2 divided doses orally).
cTarget platelet count was ≥ 90 x 10^9/L for ENABLE1 and ≥ 100 x 10^9/L for ENABLE2.
d p-value < 0.05 for eltrombopag versus placebo.

The majority of patients treated with eltrombopag (76%) maintained a platelet count greater than or equal to 50 x 10^9/L compared with 19% for placebo. A greater proportion of patients on eltrombopag did not require any antiviral dose reduction as compared with placebo (45% versus 27%).

14.3 Severe Aplastic Anemia

Refractory Severe Aplastic Anemia

Eltrombopag was studied in a single-arm, single-center, open-label trial (Study ETB115AUS28T, referred to as Study US28T [NCT00922883]) in 43 patients with severe aplastic anemia who had an insufficient response to at least one prior immunosuppressive therapy and who had a platelet count less than or equal to 30 x 10^9/L. Eltrombopag was administered at an initial dose of 50 mg once daily for 2 weeks and increased over 2-week periods up to a maximum dose of 150 mg once daily. The efficacy of eltrombopag in the study was evaluated by the hematologic response assessed after 12 weeks of treatment. Hematologic response was defined as meeting 1 or more of the following criteria: 1) platelet count increases to 20 x 10^9/L above baseline, or stable platelet counts with transfusion independence for a minimum of 8 weeks; 2) hemoglobin increase by greater than 1.5 g/dL, or a reduction in greater than or equal to 4 units of red blood cell (RBC) transfusions for 8 consecutive weeks; 3) ANC increase of 100% or an ANC increase greater than 0.5 x 10^9/L. Eltrombopag was discontinued after 16 weeks if no hematologic response was observed. Patients who responded continued therapy in an extension phase of the trial.

The treated population had median age of 45 years (range, 17 to 77 years) and 56% were male. At baseline, the median platelet count was 20 x 10^9/L, hemoglobin was 8.4 g/dL, ANC was 0.58 x 10^9/L, and absolute reticulocyte count was 24.3 x 10^9/L. Eighty-six percent of patients were red blood cell (RBC) transfusion dependent and 91% were platelet transfusion dependent. The majority of patients (84%) received at least 2 prior immunosuppressive therapies. Three patients had cytogenetic abnormalities at baseline.

Table 15 presents the efficacy results.

Table 15. Study US28T: Hematologic Response in Patients with Refractory Severe Aplastic Anemia
Outcome | Eltrombopag; n = 43
Response ratea, n (%); 95% CI (%) | 17 (40); (25, 56)
Median of duration of response in months (95% CI) | NRb (3.0, NRb)
aIncludes single- and multi-lineage.
bNR = not reached due to few events (relapsed).

In the 17 responders, the platelet transfusion-free period ranged from 8 to 1096 days with a median of 200 days, and the RBC transfusion-free period ranged from 15 to 1082 days with a median of 208 days.

In the extension phase, 8 patients achieved a multi-lineage response; 4 of these patients subsequently tapered off treatment with eltrombopag and maintained the response (median follow-up: 8.1 months, range, 7.2 to 10.6 months).

16 HOW SUPPLIED/STORAGE AND HANDLING

16.1 How Supplied

ALVAIZ (eltrombopag tablets) is for oral administration and are available as follows.

9 mg - Blue, round, biconvex, film-coated tablets debossed with “TV” on one side and “Z9” on the other side. The tablets are available in bottles of 30 (NDC 0480-3273-56).

18 mg - Off-white, round, biconvex, film-coated tablets debossed with “TV” on one side and “Z18” on the other side. The tablets are available in bottles of 30 (NDC 0480-3274-56).

36 mg - Red, round, biconvex, film-coated tablets debossed with “TV” on one side and “Z36” on the other side. The tablets are available in bottles of 30 (NDC 0480-3275-56).

54 mg - Orange, round, biconvex, film-coated tablets debossed with “TV” on one side and “Z54” on the other side. The tablets are available in bottles of 30 (NDC 0480-3276-56).

16.2 Storage and Handling

Store at 20°C to 25°C (68°F to 77°F); excursions permitted to 15°C to 30°C (59°F to 86°F) [see USP Controlled Room Temperature].

17 PATIENT COUNSELING INFORMATION

Advise the patient or caregiver to read the FDA-approved patient labeling (Medication Guide).

Prior to treatment, patients should fully understand and be informed of the following risks and considerations for ALVAIZ:

Risks

Hepatotoxicity

- Therapy with ALVAIZ may be associated with hepatobiliary laboratory abnormalities [see Warnings and Precautions (5.2)].
- Advise patients with chronic hepatitis C and cirrhosis that they may be at risk for hepatic decompensation when receiving ALVAIZ with alfa interferon therapy [see Warnings and Precautions (5.1)].
- Advise patients that they should report any of the following signs and symptoms of liver problems to their healthcare provider right away [see Warnings and Precautions (5.2)].
  - yellowing of the skin or the whites of the eyes (jaundice)
  - unusual darkening of the urine
  - unusual tiredness
  - right upper stomach area pain
  - confusion
  - swelling of the stomach area (abdomen)

Risk of Bleeding Upon ALVAIZ Discontinuation

- Advise patients that thrombocytopenia and risk of bleeding may reoccur upon discontinuing ALVAIZ, particularly if ALVAIZ is discontinued while the patient is on anticoagulants or antiplatelet agents. Advise patients that during therapy with ALVAIZ, they should continue to avoid situations or medications that may increase the risk for bleeding.

Thrombotic/Thromboembolic Complications

- Advise patients that too much ALVAIZ may result in excessive platelet counts and a risk for thrombotic/thromboembolic complications [see Warnings and Precautions (5.4)].

Cataracts

- Advise patients to have a baseline ocular examination prior to administration of ALVAIZ and be monitored for signs and symptoms of cataracts during therapy [see Warnings and Precautions (5.5)].

Drug Interactions

- Advise patients to take ALVAIZ at least 2 hours before or 4 hours after calcium-rich foods, mineral supplements, and antacids which contain polyvalent cations, such as iron, calcium, aluminum, magnesium, selenium, and zinc [see Dosage and Administration (2.4), Drug Interactions (7.1)].

Lactation

- Advise women not to breastfeed during treatment with ALVAIZ [see Use in Specific Populations (8.2)].

Administration of ALVAIZ

- For patients with persistent or chronic ITP, therapy with ALVAIZ is administered to achieve and maintain a platelet count greater than or equal to 50 x 10^9/L as necessary to reduce the risk for bleeding [see Indications and Usage (1.1)].
- For patients with chronic hepatitis C, therapy with ALVAIZ is administered to achieve and maintain a platelet count necessary to initiate and maintain antiviral therapy with pegylated interferon and ribavirin [see Indications and Usage (1.2)].
- Advise patients to take ALVAIZ without a meal or with a meal low in calcium (≤ 50 mg) and at least 2 hours before or 4 hours after other medications (e.g., antacids) and calcium-rich foods [see Dosage and Administration (2.4)].

Brands listed are the trademarks of their respective owners.

Manufactured For:
Teva Pharmaceuticals
Parsippany, NJ 07054

Rev. C 1/2026

MEDICATION GUIDE

ALVAIZ® (al-VAYZ)

(eltrombopag) tablets

What is the most important information I should know about ALVAIZ?

ALVAIZ may cause serious side effects, including:

Liver problems:

- If you have chronic hepatitis C virus and take ALVAIZ with interferon and ribavirin treatment, ALVAIZ may increase your risk of liver problems. If your healthcare provider tells you to stop your treatment with interferon and ribavirin, you will also need to stop taking ALVAIZ.
- ALVAIZ may increase your risk of liver problems that may be severe and possibly life threatening. Your healthcare provider will do blood tests to check your liver function before you start taking ALVAIZ and during your treatment. Your healthcare provider may stop your treatment with ALVAIZ if you have changes in your liver function blood tests.

Tell your healthcare provider right away if you have any of these signs and symptoms of liver problems:

- yellowing of the skin or the whites of the eyes (jaundice)
- unusual darkening of the urine
- unusual tiredness

- right upper stomach area (abdomen) pain
- confusion
- swelling of the stomach area (abdomen)

See “What are the possible side effects of ALVAIZ?” for other side effects of ALVAIZ.

What is ALVAIZ?

ALVAIZ is a prescription medicine used to treat:

- adults and children 6 years of age and older with low blood platelet counts due to persistent or chronic immune thrombocytopenia (ITP), when other medicines to treat ITP or surgery to remove the spleen have not worked well enough.
- adults with
  - low blood platelet counts due to chronic hepatitis C virus (HCV) infection before and during treatment with interferon.
  - severe aplastic anemia (SAA) when other medicines to treat SAA have not worked well enough.

ALVAIZ is used to try to raise platelet counts in order to lower your risk for bleeding.

ALVAIZ is not used to make platelet counts normal.

ALVAIZ is not for use in people with a pre-cancerous condition called myelodysplastic syndrome (MDS), or in people with low platelet counts caused by certain other medical conditions or diseases.

It is not known if ALVAIZ is safe and effective when used with other antiviral medicines to treat chronic hepatitis C.

It is not known if ALVAIZ is safe and effective in children:

- younger than 6 years with persistent or chronic ITP
- with low blood platelet counts due to chronic hepatitis C
- whose severe aplastic anemia (SAA) has not improved after previous treatments

Before you take ALVAIZ, tell your healthcare provider about all of your medical conditions, including if you:

- have liver problems
- have a precancerous condition called MDS or a blood cancer
- have or had a blood clot
- have a history of cataracts
- have had surgery to remove your spleen (splenectomy)
- have bleeding problems
- are of East-Asian or Southeast-Asian ancestry. You may need a lower dose of ALVAIZ.
- are pregnant or plan to become pregnant. It is not known if ALVAIZ will harm an unborn baby. Tell your healthcare provider if you become pregnant or think you may be pregnant during treatment with ALVAIZ.
  - Females who are able to become pregnant, should use effective birth control (contraception) during treatment with ALVAIZ and for at least 7 days after stopping treatment with ALVAIZ. Talk to your healthcare provider about birth control methods that may be right for you during this time.
- are breastfeeding or plan to breastfeed. You should not breastfeed during your treatment with ALVAIZ. Talk to your healthcare provider about the best way to feed your baby during this time.

Tell your healthcare provider about all the medicines you take, including prescription and over-the-counter medicines, vitamins, and herbal supplements. ALVAIZ may affect the way certain medicines work. Certain other medicines may affect the way ALVAIZ works.

Especially tell your healthcare provider if you take:

- certain medicines used to treat high cholesterol, called “statins”
- a blood thinner medicine

Certain medicines may keep ALVAIZ from working correctly. Take ALVAIZ at least 2 hours before or 4 hours after taking these products:

- antacid medicine used to treat stomach ulcers or heartburn
- multivitamins or products that contain iron, calcium, aluminum, magnesium, selenium, and zinc which may be found in mineral supplements.

Ask your healthcare provider if you are not sure if your medicine is one that is listed above.

Know the medicines you take. Keep a list of them and show it to your healthcare provider and pharmacist when you get a new medicine.

How should I take ALVAIZ?

- Take ALVAIZ exactly as your healthcare provider tells you to take it. Your healthcare provider will prescribe the dose of ALVAIZ tablets.
- Swallow ALVAIZ tablets whole. Do not split, chew, or crush ALVAIZ tablets and do not mix with food or liquids. Tell your healthcare provider if your or your child are not able to swallow ALVAIZ tablets whole. You will need to take a different medicine.
- Do not stop taking ALVAIZ without talking with your healthcare provider first. Do not change your dose or schedule for taking ALVAIZ unless your healthcare provider tells you to change it.
- The dose of ALVAIZ is not the same as other eltrombopag products. Do not change between ALVAIZ and other eltrombopag products unless your healthcare provider tells you.
- Take ALVAIZ without a meal or with a meal low in calcium (50 mg or less) and at least 2 hours before or 4 hours after eating calcium-rich foods, such as dairy products, calcium-fortified juices, and certain fruits and vegetables.
- Do not take more than 1 dose of ALVAIZ in 1 day.
- If you take too much ALVAIZ, you may have a higher risk of serious side effects. Call your healthcare provider right away.
- Your healthcare provider will check your platelet count during your treatment with ALVAIZ and change your dose of ALVAIZ as needed.
- Tell your healthcare provider about any bruising or bleeding that happens during treatment and after you stop taking ALVAIZ.
- If you have SAA, your healthcare provider may do tests to monitor your bone marrow during treatment with ALVAIZ.

What should I avoid while taking ALVAIZ?

Avoid situations and medicines that may increase your risk of bleeding during treatment with ALVAIZ.

What are the possible side effects of ALVAIZ?

ALVAIZ may cause serious side effects, including:

- See “What is the most important information I should know about ALVAIZ?”
- Increased risk of worsening of a precancerous blood condition called myelodysplastic syndrome (MDS) to acute myelogenous leukemia (AML). ALVAIZ is not for use in people with a precancerous condition called myelodysplastic syndromes (MDS). See “What is ALVAIZ?” If you have MDS and receive ALVAIZ, you have an increased risk that your MDS condition may worsen and become a blood cancer called AML. If your MDS worsens to become AML, you may have an increased risk of death from AML.
- High platelet counts and higher risk for blood clots. Your risk of getting a blood clot is increased if your platelet count is too high during treatment with ALVAIZ. Your risk of getting a blood clot may also be increased during treatment with ALVAIZ if you have normal or low platelet counts. You may have severe problems or die from some forms of blood clots, such as clots that travel to the lungs or that cause heart attacks or strokes. Your healthcare provider will check your blood platelet counts, and change your dose or stop ALVAIZ if your platelet counts get too high. Tell your healthcare provider right away if you have signs and symptoms of a blood clot in the leg, such as swelling, pain, or tenderness in your leg.
  People with chronic liver disease may be at risk for a type of blood clot in the stomach area (abdomen). Tell your healthcare provider right away if you have stomach-area (abdomen) pain, nausea, vomiting, or diarrhea as these may be symptoms of this type of blood clot.
- New or worsened cataracts (a clouding of the lens in the eye). New or worsened cataracts can happen in people taking ALVAIZ. Your healthcare provider will check your eyes before and during your treatment with ALVAIZ. Tell your healthcare provider about any changes in your eyesight during treatment with ALVAIZ.

The most common side effects of ALVAIZ in adults and children include:

- low red blood cell count (anemia)
- nausea
- fever
- abnormal liver function tests

- cough
- tiredness
- headache
- diarrhea

Laboratory tests may show abnormal changes to the cells in your bone marrow.

Tell your healthcare provider if you have any side effect that bothers you or that does not go away. These are not all of the possible side effects of ALVAIZ. For more information, ask your healthcare provider or pharmacist.

Call your doctor for medical advice about side effects. You may report side effects to FDA at 1-800-FDA-1088.

How should I store ALVAIZ tablets?

- Store ALVAIZ tablets at room temperature between 68°F to 77°F (20°C to 25°C). Keep ALVAIZ in the bottle given to you.

Keep ALVAIZ and all medicines out of the reach of children.

General information about the safe and effective use of ALVAIZ.

Medicines are sometimes prescribed for purposes other than those listed in a Medication Guide. Do not use ALVAIZ for a condition for which it was not prescribed. Do not give ALVAIZ to other people, even if they have the same symptoms that you have. It may harm them.

You can ask your pharmacist or healthcare provider for information about ALVAIZ that is written for health professionals.

What are the ingredients in ALVAIZ?

Active ingredient: eltrombopag choline

Inactive ingredients:

Tablet Core: anhydrous lactose, copovidone, croscarmellose sodium, edetate disodium dihydrate, magnesium stearate, poloxamer 188, polyethylene glycol 4000, povidone K12, silicified microcrystalline cellulose, and silicon dioxide

Coating:

- 9 mg tablets: FD&C Blue No. 1 aluminum lake, polyethylene glycol 3350, polyvinyl alcohol, talc, and titanium dioxide.
- 18 mg tablets: Hypromellose 2910, polyethylene glycol 4000, talc, and titanium dioxide.
- 36 mg tablets: Iron oxide red, iron oxide yellow, polyethylene glycol 3350, polyvinyl alcohol, talc, and titanium dioxide.
- 54 mg tablets: FD&C Red #40 aluminum lake, hypromellose 2910, iron oxide yellow, polyethylene glycol 400, and titanium dioxide.

Manufactured For: Teva Pharmaceuticals, Parsippany, NJ 07054

For more information about call Teva at 1-888-838-2872.

This Medication Guide has been approved by the U.S. Food and Drug Administration. Rev. C 1/2026

PACKAGE.LABEL.PRINCIPAL DISPLAY PANEL

NDC 0480-3273-56

Rx only

Alvaiz® (eltrombopag tablets)

9 mg*

PHARMACIST: Dispense the accompanying Medication Guide to each patient.

Alvaiz is NOT substitutable with other eltrombopag products on a milligram-per-milligram basis.

30 Tablets

PACKAGE LABEL.PRINCIPAL DISPLAY PANEL

NDC 0480-3274-56

Rx only

Alvaiz® (eltrombopag tablets)

18 mg*

PHARMACIST: Dispense the accompanying Medication Guide to each patient.

Alvaiz is NOT substitutable with other eltrombopag products on a milligram-per-milligram basis.

30 Tablets

PACKAGE LABEL.PRINCIPAL DISPLAY PANEL

NDC 0480-3275-56

Rx only

Alvaiz® (eltrombopag tablets)

36 mg*

PHARMACIST: Dispense the accompanying Medication Guide to each patient.

Alvaiz is NOT substitutable with other eltrombopag products on a milligram-per-milligram basis.

30 Tablets

PACKAGE LABEL.PRINCIPAL DISPLAY PANEL

NDC 0480-3276-56

Rx only

Alvaiz® (eltrombopag tablets)

54 mg*

PHARMACIST: Dispense the accompanying Medication Guide to each patient.

Alvaiz is NOT substitutable with other eltrombopag products on a milligram-per-milligram basis.

30 Tablets